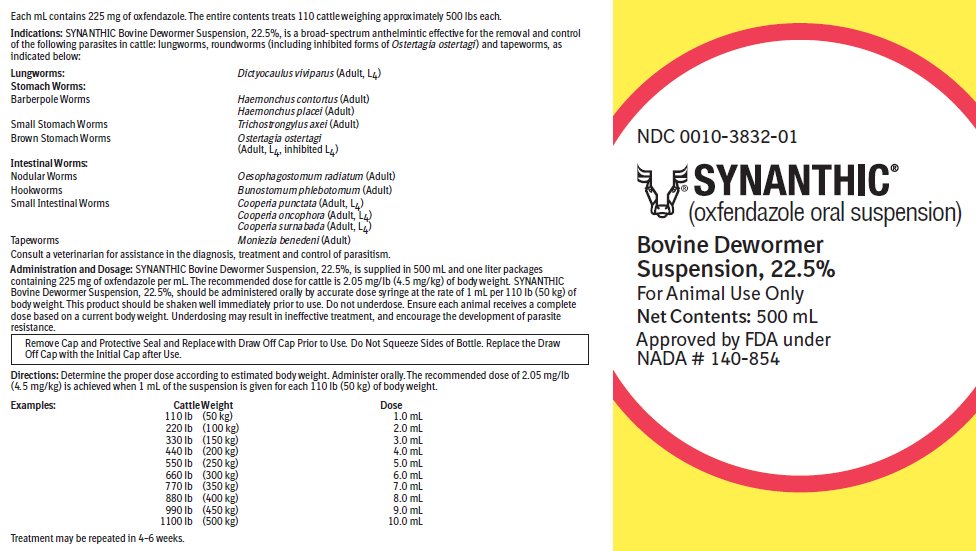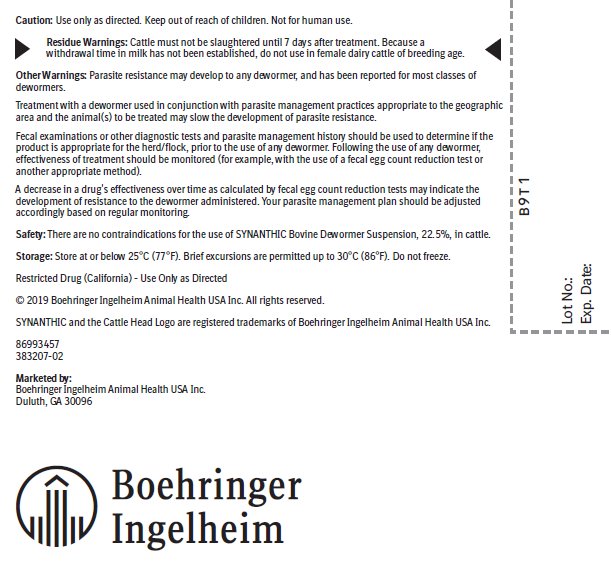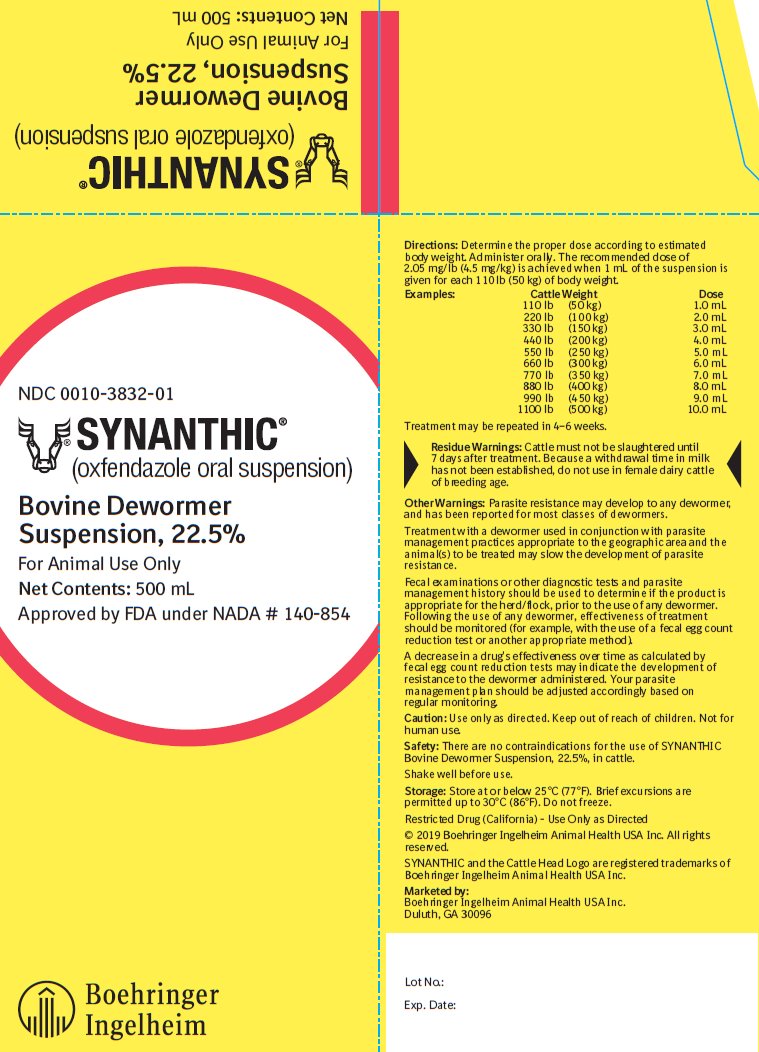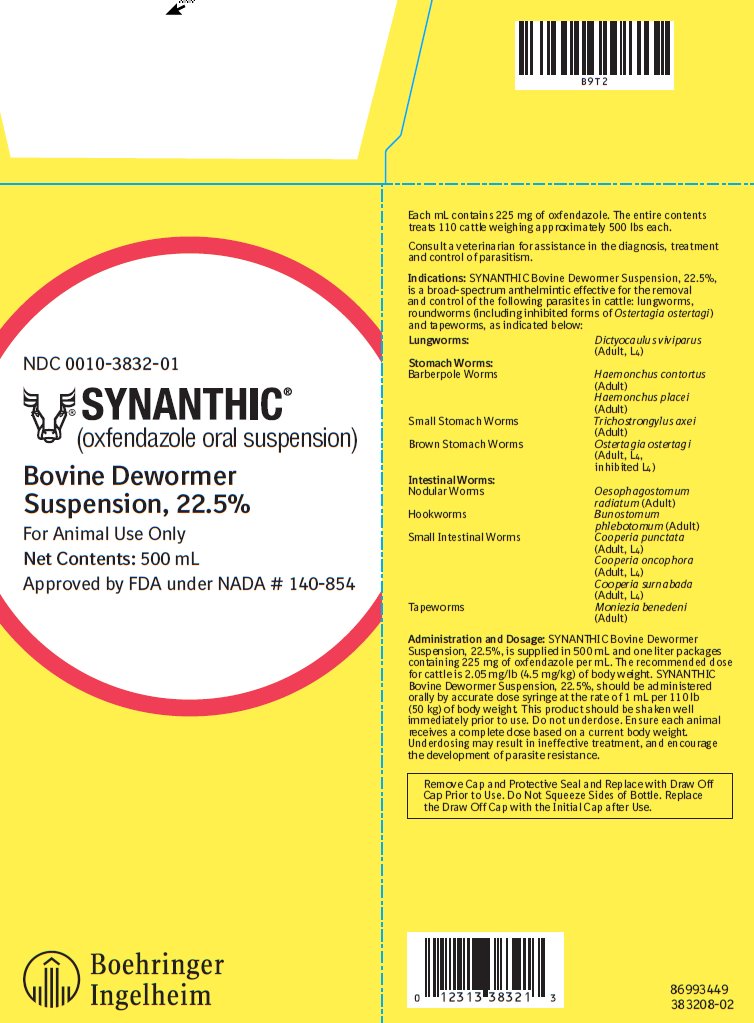 DRUG LABEL: Synanthic Bovine Dewormer
NDC: 0010-3832 | Form: SUSPENSION
Manufacturer: Boehringer Ingelheim Animal Health USA Inc.
Category: animal | Type: OTC ANIMAL DRUG LABEL
Date: 20250501

ACTIVE INGREDIENTS: OXFENDAZOLE 225 mg/1 mL

Synanthic®
(oxfendazole oral suspension)
Bovine Dewormer
Suspension, 22.5%

DESCRIPTION

Each mL contains 225 mg of oxfendazole.

The entire contents of the 500 mL bottle treats 110 cattle weighing approximately 500 lbs each.

The entire contents of the 1000 mL bottle treats 220 cattle weighing approximately 500 lbs each.

Consult a veterinarian for assistance in the diagnosis, treatment and control of parasitism.

Indications:

SYNANTHIC Bovine Dewormer Suspension, 22.5%, is a broad-spectrum anthelmintic effective for the removal and control of the following parasites in cattle: lungworms, roundworms (including inhibited forms of Ostertagia ostertagi) and tapeworms, as indicated below:

Lungworms: | Dictyocaulus viviparus (Adult, L4)
Stomach Worms:
Barberpole Worms | Haemonchus contortus (Adult)
 | Haemonchus placei (Adult)
Small Stomach Worms | Trichostrongylus axei (Adult)
Brown Stomach Worms | Ostertagia ostertagi (Adult, L4, inhibited L4)
Intestinal Worms:
Nodular Worms | Oesophagostomum radiatum (Adult)
Hookworms | Bunostomum phlebotomum (Adult)
Small Intestinal Worms | Cooperia punctata (Adult, L4)
 | Cooperia oncophora (Adult, L4)
 | Cooperia surnabada (Adult, L4)
Tapeworms | Moniezia benedeni (Adult)

Administration and Dosage:

SYNANTHIC Bovine Dewormer Suspension, 22.5%, is supplied in 500 mL and one liter packages containing 225 mg of oxfendazole per mL. The recommended dose for cattle is 2.05 mg/lb (4.5 mg/kg) of body weight. SYNANTHIC Bovine Dewormer Suspension, 22.5%, should be administered orally by accurate dose syringe at the rate of 1 mL per 110 lb (50 kg) of body weight. This product should be shaken well immediately prior to use. Do not underdose. Ensure each animal receives a complete dose based on a current body weight. Underdosing may result in ineffective treatment, and encourage the development of parasite resistance.

Remove Cap and Protective Seal and Replace with Draw Off Cap Prior to Use. Do Not Squeeze Sides of Bottle. Replace the Draw Off Cap with the Initial Cap after Use.

Directions:

Determine the proper dose according to estimated body weight. Administer orally. The recommended dose of 2.05 mg/lb (4.5 mg/kg) is achieved when 1 mL of the suspension is given for each 110 lb (50 kg) of body weight.

Examples:

Cattle Weight | Dose
110 lb (50 kg) | 1.0 mL
220 lb (100 kg) | 2.0 mL
330 lb (150 kg) | 3.0 mL
440 lb (200 kg) | 4.0 mL
550 lb (250 kg) | 5.0 mL
660 lb (300 kg) | 6.0 mL
770 lb (350 kg) | 7.0 mL
880 lb (400 kg) | 8.0 mL
990 lb (450 kg) | 9.0 mL
1100 lb (500 kg) | 10.0 mL

Treatment may be repeated in 4–6 weeks.

Residue Warnings:

Cattle must not be slaughtered until 7 days after treatment. Because a withdrawal time in milk has not been established, do not use in female dairy cattle of breeding age.

Other Warnings

Parasite resistance may develop to any dewormer, and has been reported for most classes of dewormers.

Treatment with a dewormer used in conjunction with parasite management practices appropriate to the geographic area and the animal(s) to be treated may slow the development of parasite resistance.

Fecal examinations or other diagnostic tests and parasite management history should be used to determine if the product is appropriate for the herd/flock, prior to the use of any dewormer. Following the use of any dewormer, effectiveness of treatment should be monitored (for example, with the use of a fecal egg count reduction test or another appropriate method).

A decrease in a drug's effectiveness over time as calculated by fecal egg count reduction tests may indicate the development of resistance to the dewormer administered. Your parasite management plan should be adjusted accordingly based on regular monitoring.

Caution:

Use only as directed. Keep out of reach of children. Not for human use.

Safety:

There are no contraindications for the use of SYNANTHIC Bovine Dewormer Suspension, 22.5%, in cattle.

Shake well before use.

Storage:

Store at or below 25°C (77°F). Brief excursions are permitted up to 30°C (86°F). Do not freeze.

Restricted Drug (California) – Use Only as Directed

© 2019 Boehringer Ingelheim Animal Health USA Inc. All rights reserved.

SYNANTHIC and the Cattle Head Logo are registered trademarks of Boehringer Ingelheim Animal Health USA Inc.

86993449

383208-02

Marketed by:
Boehringer Ingelheim Animal Health USA Inc.
Duluth, GA 30096

Principal Display Panel – Container Label 500 mL

NDC 0010-3832-01

SYNANTHIC®

(oxfendazole oral suspension)

Bovine Dewormer Suspension, 22.5%

For Animal Use Only

Net Contents: 500 mL

Approved by FDA under NADA # 140-854

Principal Display Panel – Display Carton 500 mL

NDC 0010-3832-01

SYNANTHIC®

(oxfendazole oral suspension)

Bovine Dewormer Suspension, 22.5%

For Animal Use Only

Net Contents: 500 mL

Approved by FDA under NADA # 140-854